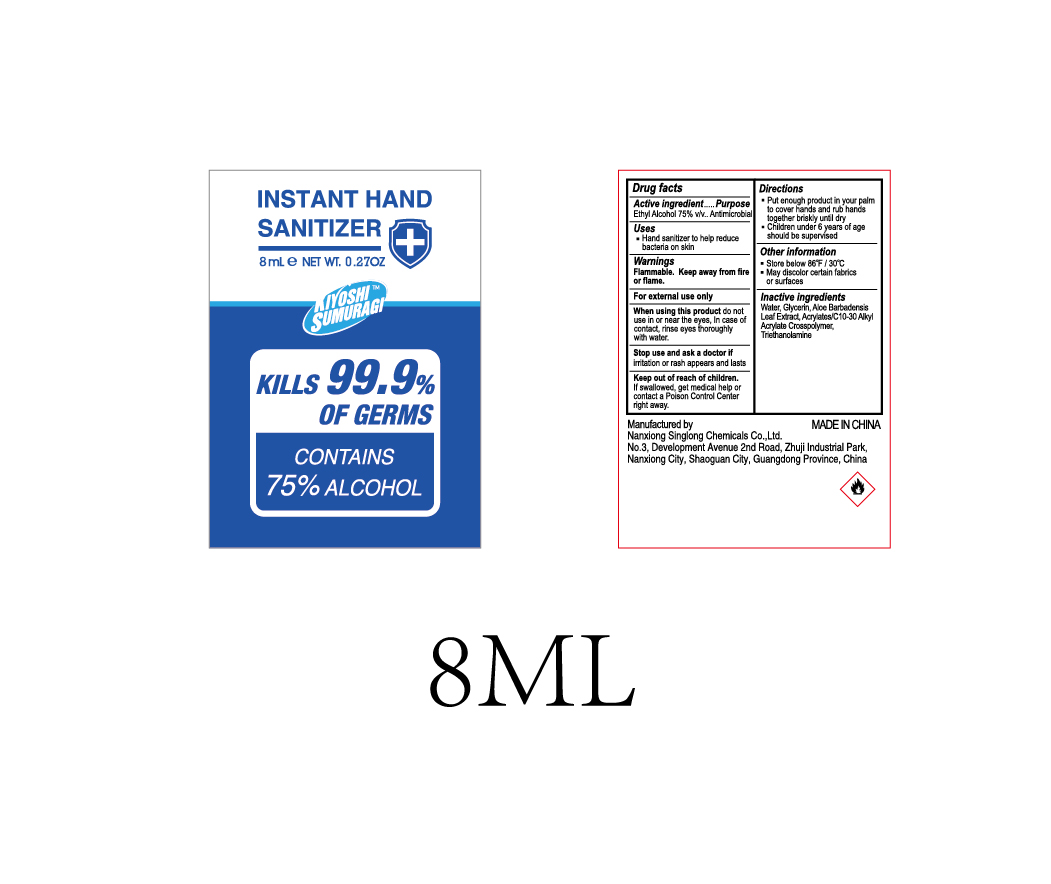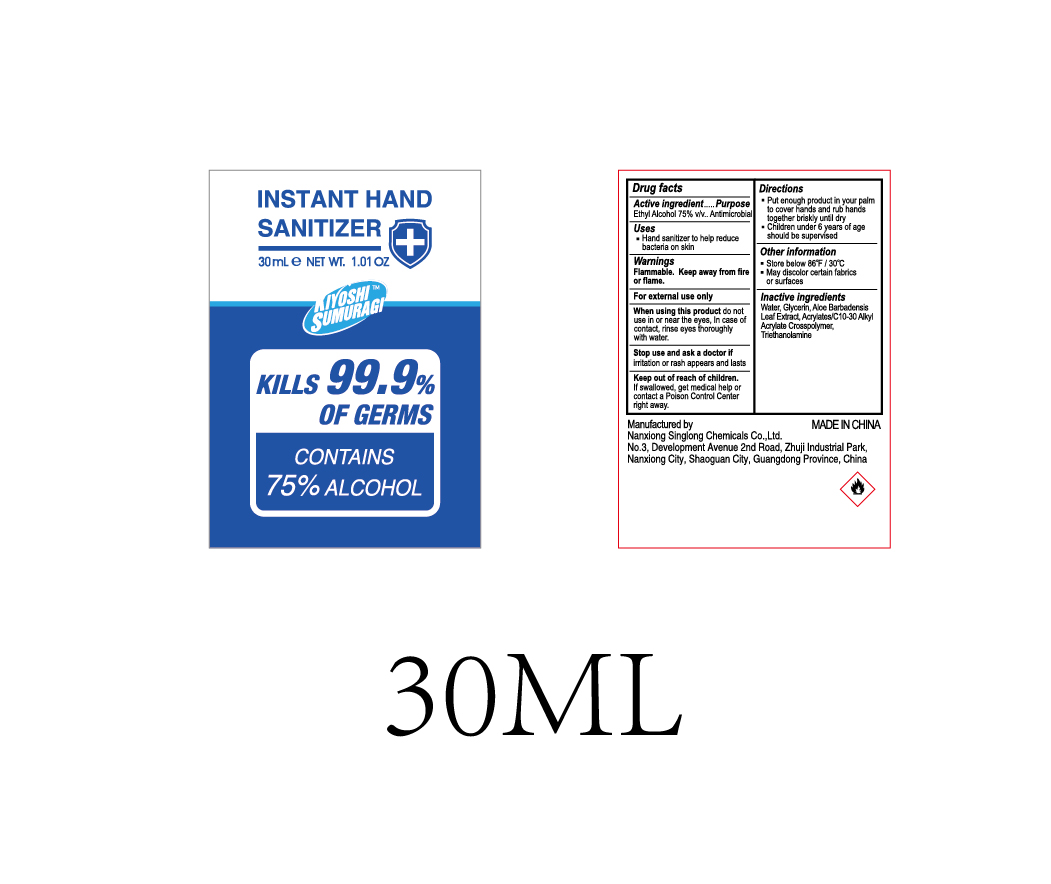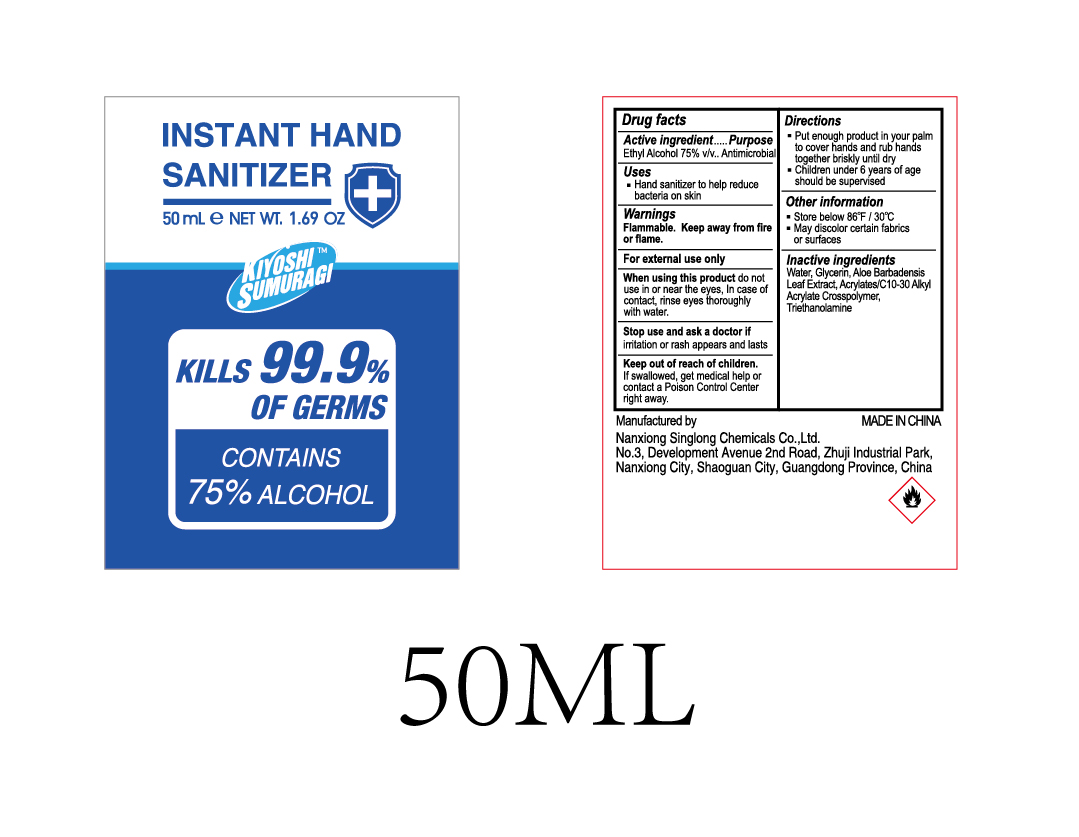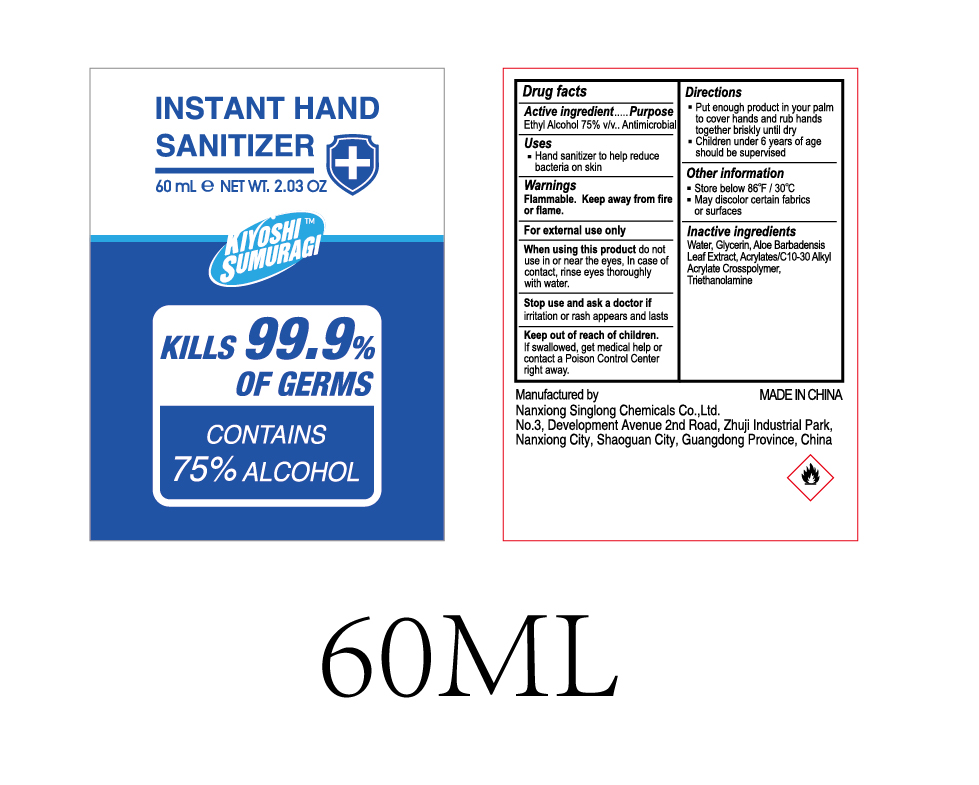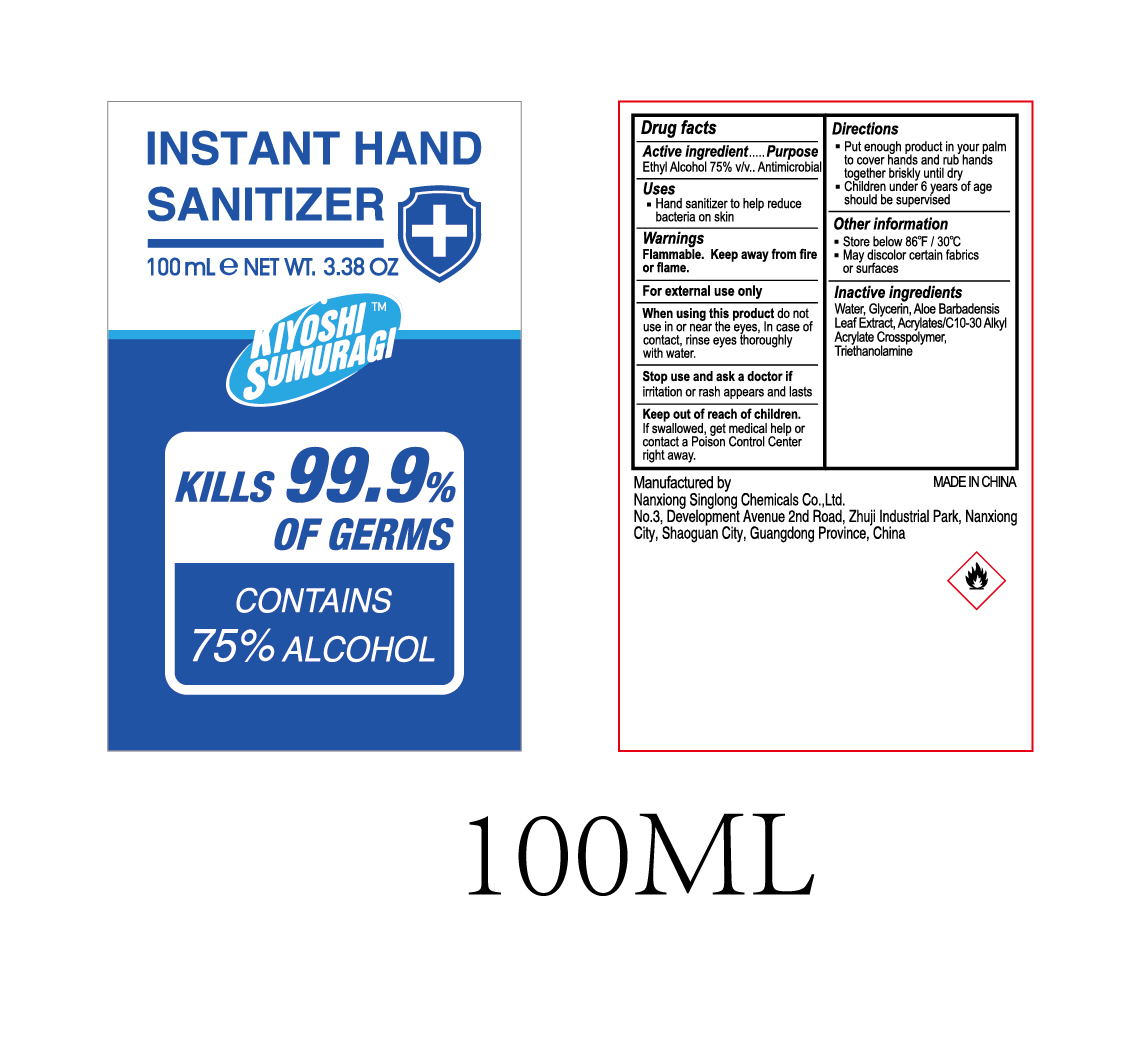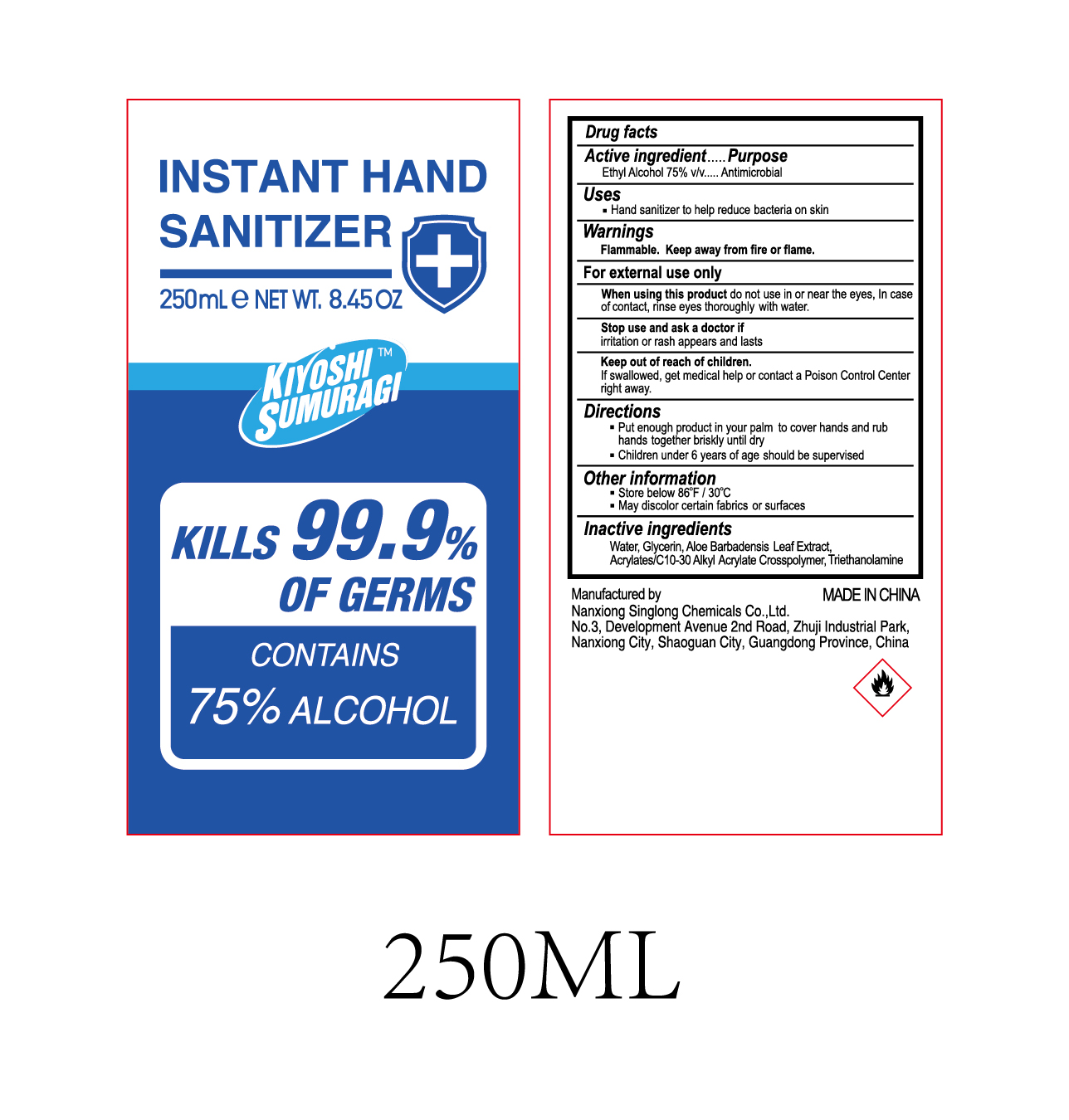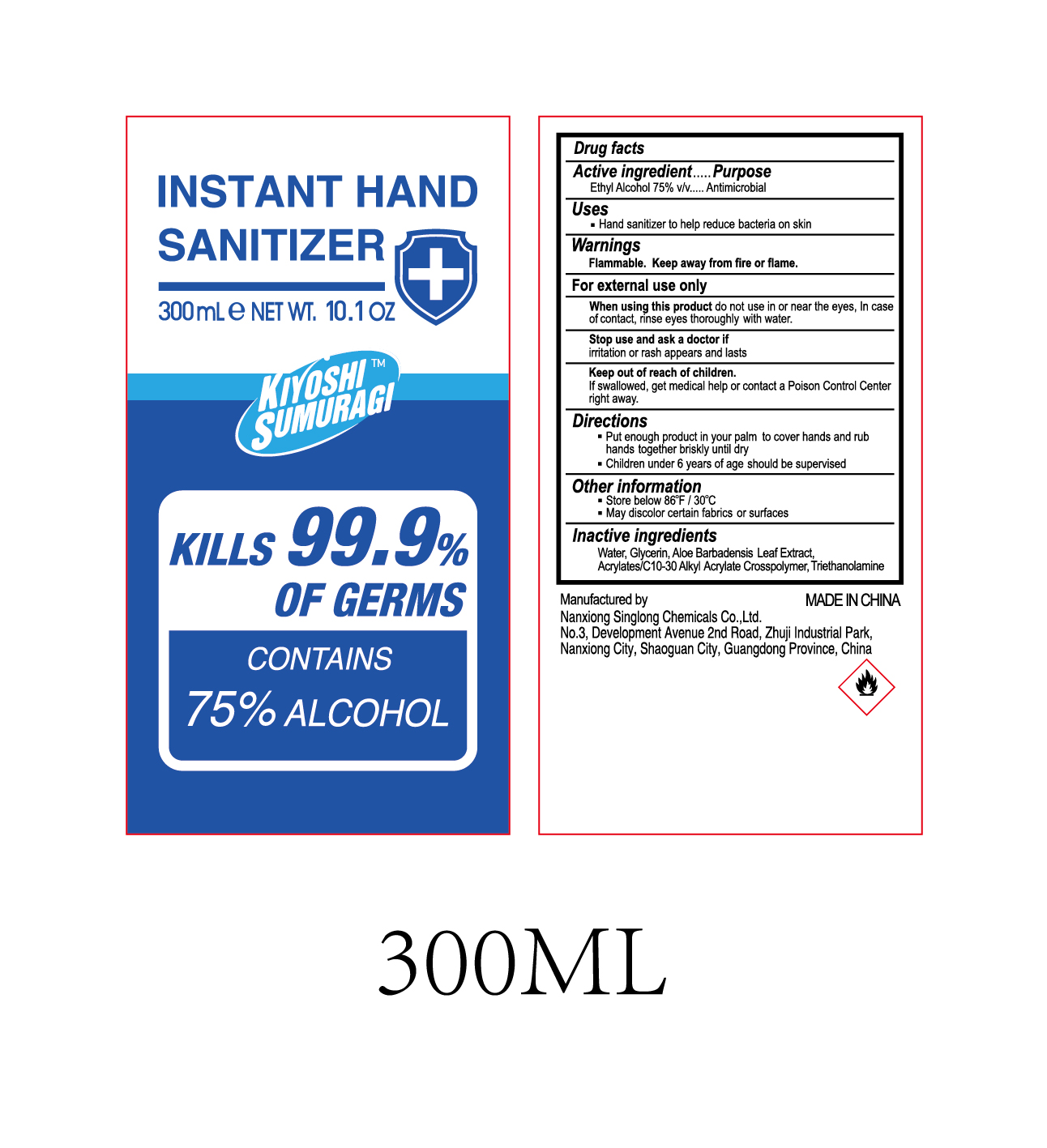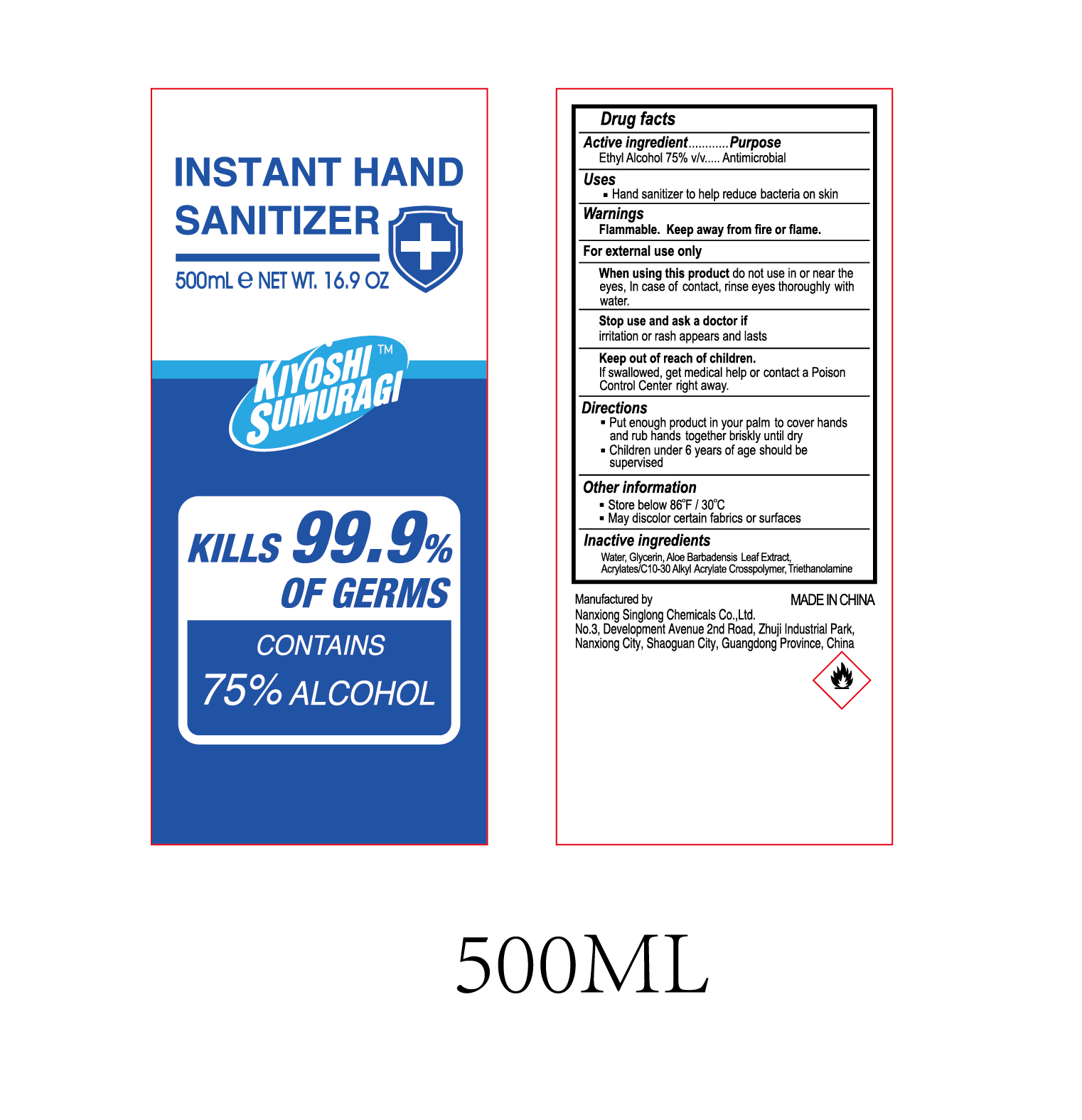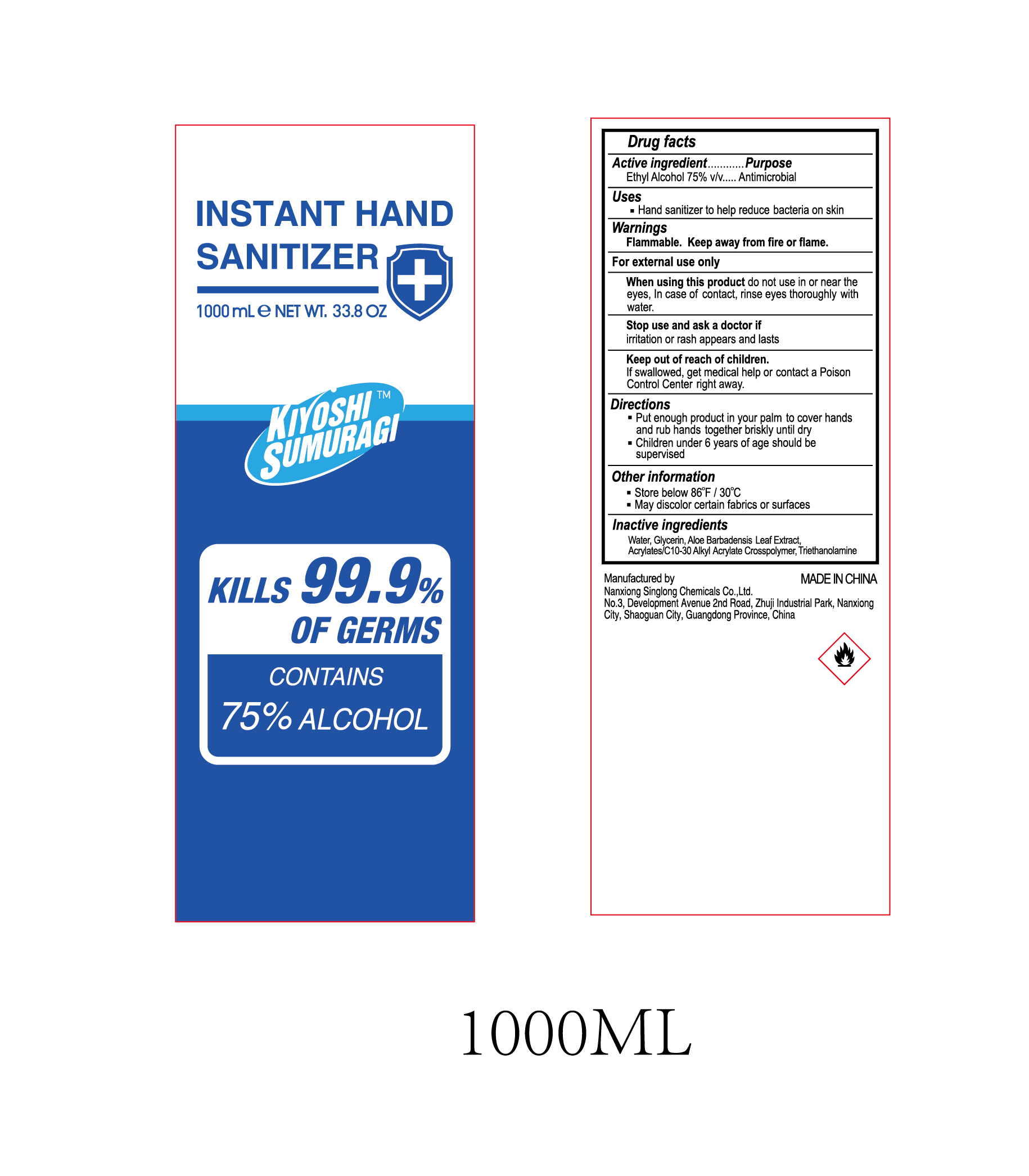 DRUG LABEL: INSTANT HAND SANITIZER
NDC: 80533-001 | Form: GEL
Manufacturer: NANXIONG SINGLONG CHEMICALS CO.,LTD.
Category: otc | Type: HUMAN OTC DRUG LABEL
Date: 20200905

ACTIVE INGREDIENTS: ALCOHOL 75 mL/100 mL
INACTIVE INGREDIENTS: GLYCERIN; ALOE VERA LEAF; WATER; TROLAMINE; CARBOMER INTERPOLYMER TYPE A (55000 CPS)

80533-001
INSTANT HAND SANITIZER

Active Ingredient(s)

Ethyl Alcohol 75%v/v

Purpose

Antimicrobial

Use

Hand sanitizer to help reduce bacteria on skin

Warnings

Flammable. Keep away from fire or flame.
For external use only

When using this product do not use in or near the eyes, In case of contact, rinse eyes thoroughly with water.

Stop use and ask a doctor if irritation or rash appears and lasts

Keep out of reach of children.
If swallowed, get medical help or contact a Poison
Control Center right away.

do not use in or near the eyes, In case of contact, rinse eyes thoroughly with water.

When using this product do not use in or near the eyes, In case of contact, rinse eyes thoroughly with water.

Stop use and ask a doctor if irritation or rash appears and lasts

Keep out of reach of children.
If swallowed, get medical help or contact a Poison
Control Center right away.

Stop use and ask a doctor if irritation or rash appears and lasts

Keep out of reach of children.
If swallowed, get medical help or contact a Poison
Control Center right away.

Directions

Put enough product in your palm to cover hands and rub hands together briskly until dry
Children under 6 years of age should be supervised

Other information

Store below 86°F/30°C
May discolor certain fabrics or surfaces

Inactive ingredients

water, Glycerin, Aloe Barbadensis Leaf Extract, Acry1ates/C10-30 Alkyl Acrylate Crosspolymer, Triethanolamine